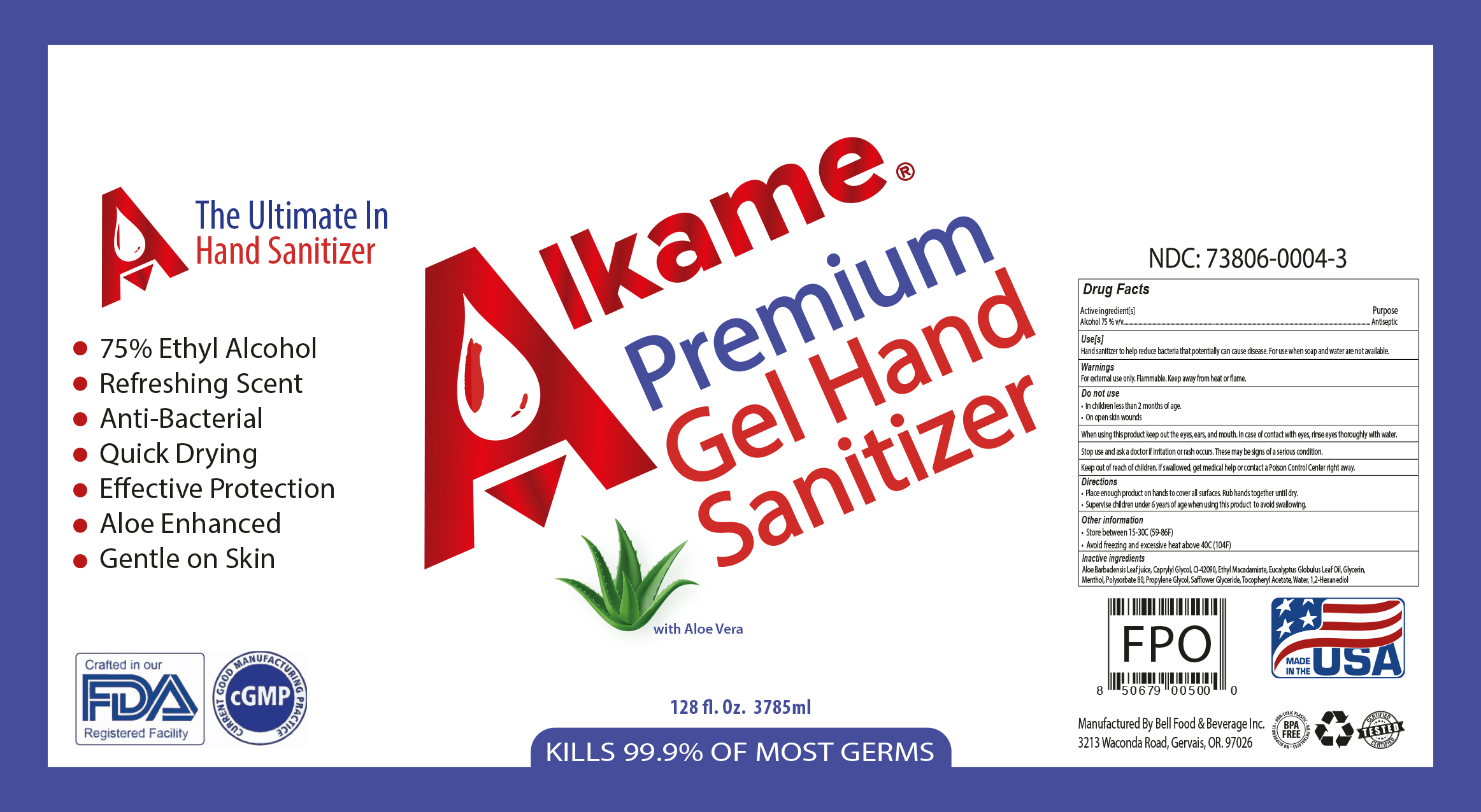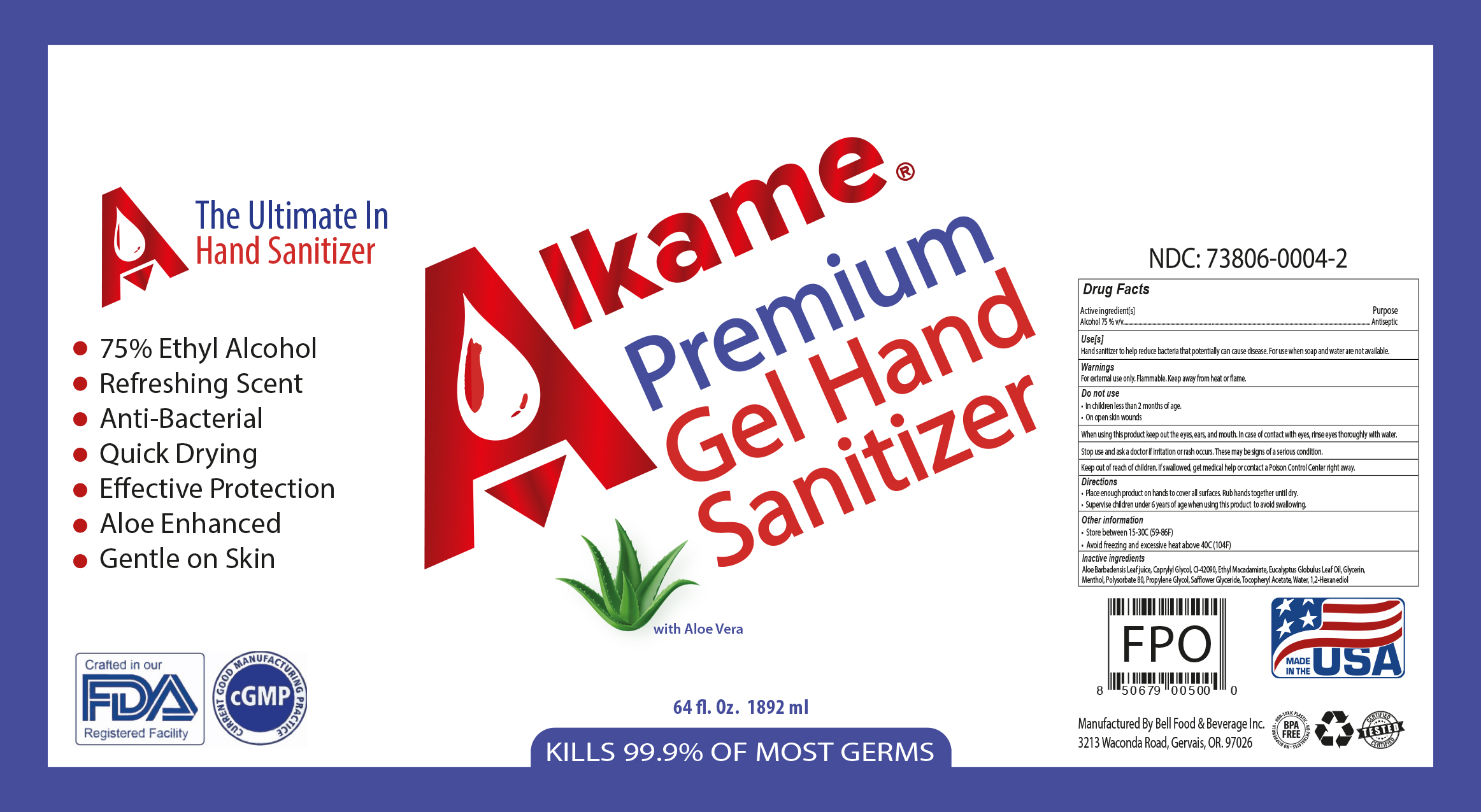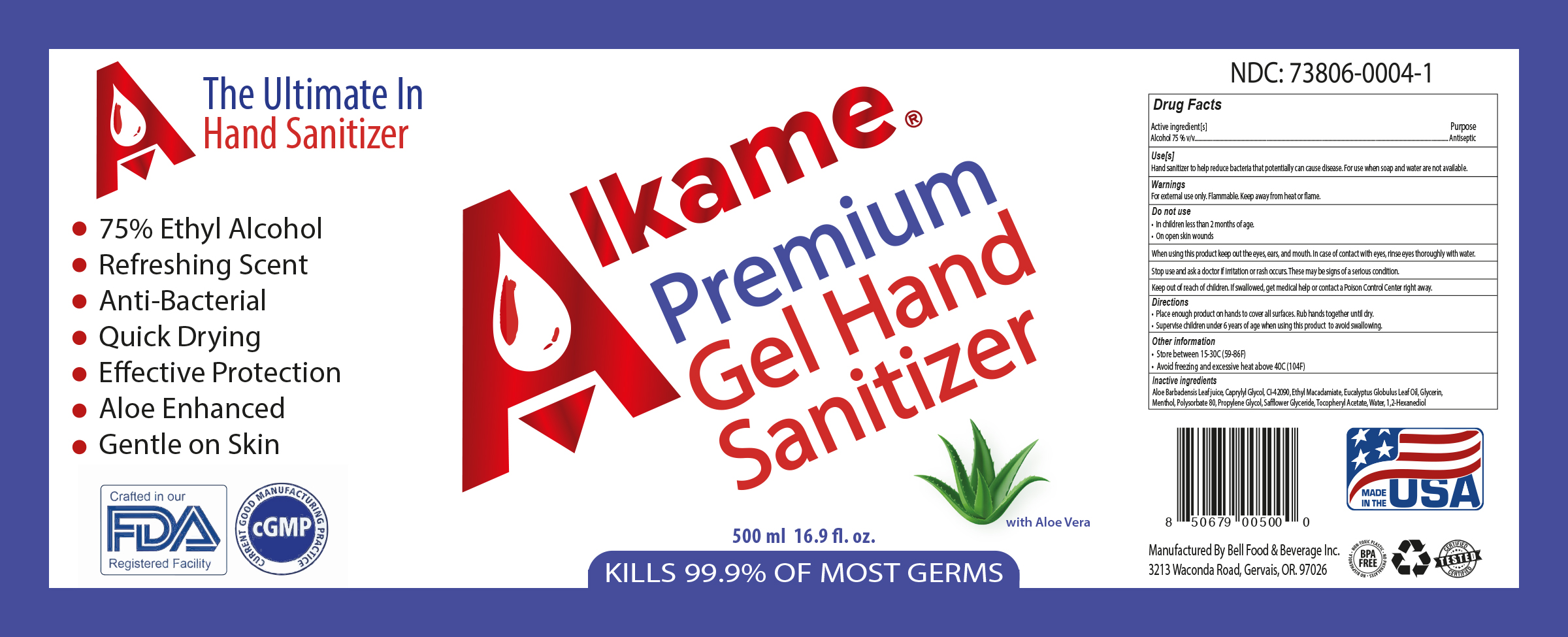 DRUG LABEL: Hand Sanitizer
NDC: 73806-0004 | Form: GEL
Manufacturer: Bell Food & Beverage Inc.
Category: otc | Type: HUMAN OTC DRUG LABEL
Date: 20201120

ACTIVE INGREDIENTS: ALCOHOL 75 mL/100 mL
INACTIVE INGREDIENTS: ETHYL MACADAMIATE; MENTHOL, UNSPECIFIED FORM; POLYSORBATE 80; SAFFLOWER OIL; EUCALYPTUS OIL; .ALPHA.-TOCOPHEROL ACETATE; FD&C BLUE NO. 1; CAPRYLYL GLYCOL; WATER; ALOE VERA LEAF; PROPYLENE GLYCOL; 1,2-HEXANEDIOL; GLYCERIN

Active Ingredient(s)

Alcohol 75% v/v. Purpose: Antiseptic

Purpose

Antiseptic

Use[s]

Hand Sanitizer to help reduce bacteria that potentially can cause disease. For use when soap and water are not available.

Warnings

For external use only. Flammable. Keep away from heat or flame

Do not use

- in children less than 2 months of age
- on open skin wounds

When using this product keep out of eyes, ears, and mouth. In case of contact with eyes, rinse eyes thoroughly with water.
Stop use and ask a doctor if irritation or rash occurs. These may be signs of a serious condition.
Keep out of reach of children. If swallowed, get medical help or contact a Poison Control Center right away.

Stop use and ask a doctor if irritation or rash occurs. These may be signs of a serious condition.

Keep out of reach of children. If swallowed, get medical help or contact a Poison Control Center right away.

Directions

- Place enough product on hands to cover all surfaces. Rub hands together until dry.
- Supervise children under 6 years of age when using this product to avoid swallowing.

Other information

- Store between 15-30C (59-86F)
- Avoid freezing and excessive heat above 40C (104F)

Inactive ingredients

Aloe Barbadensis Leaf Juice, Caprylyl Glycol, CI-42090, Ethyl Macadamiate, Eucalyptus Globulus Leaf Oil, Glycerin, Menthol, Polysorbate 80, Propylene Glycol, Safflower Glyceride, Tocopheryl Acetate, Water, 1,2-Hexanediol

Package Label - Principal Display Panel

500 mL NDC: 73806-0004-1

1892 mL NDC: 73806-0004-2

3785mL NDC: 73806-0004-3